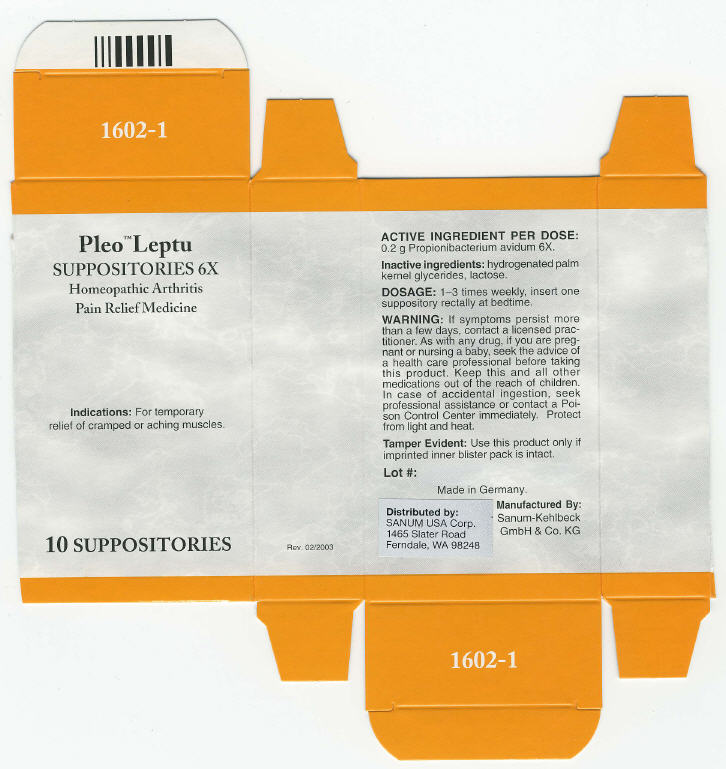 DRUG LABEL: Pleo Leptu
NDC: 60681-1602 | Form: SUPPOSITORY
Manufacturer: Sanum Kehlbeck GmbH & Co. KG
Category: homeopathic | Type: HUMAN OTC DRUG LABEL
Date: 20091013

ACTIVE INGREDIENTS: propionibacterium avidum 6 [HP_X]/1 1
INACTIVE INGREDIENTS: lactose

Pleo™ Leptu
SUPPOSITORIES 6X

Homeopathic Arthritis Pain Relief Medicine

10 SUPPOSITORIES

Indications

For temporary relief of cramped or aching muscles.

ACTIVE INGREDIENT PER DOSE

0.2 g Propionibacterium avidum 6X.

Inactive ingredients

hydrogenated palm kernel glycerides, lactose.

DOSAGE

1–3 times weekly, insert one suppository rectally at bedtime.

WARNING

If symptoms persist more than a few days, contact a licensed practitioner. As with any drug, if you are pregnant or nursing a baby, seek the advice of a health care professional before taking this product.

KEEP OUT OF REACH OF CHILDREN

Keep this and all other medications out of the reach of children. In case of accidental ingestion, seek professional assistance or contact a Poison Control Center immediately.

STORAGE AND HANDLING

Protect from light and heat.

Tamper Evident

Use this product only if imprinted inner blister pack is intact.

Made in Germany.

Distributed by:
SANUM USA Corp.
1465 Slater Road
Ferndale, WA 98248

Manufactured By:
Sanum-Kehlbeck
GmbH & Co. KG

Rev. 02/2003

PRINCIPAL DISPLAY PANEL - 10 Suppositories Carton

Pleo™ Leptu
SUPPOSITORIES 6X

Homeopathic Arthritis
Pain Relief Medicine

Indications: For temporary
relief of cramped or aching muscles.

10 SUPPOSITORIES